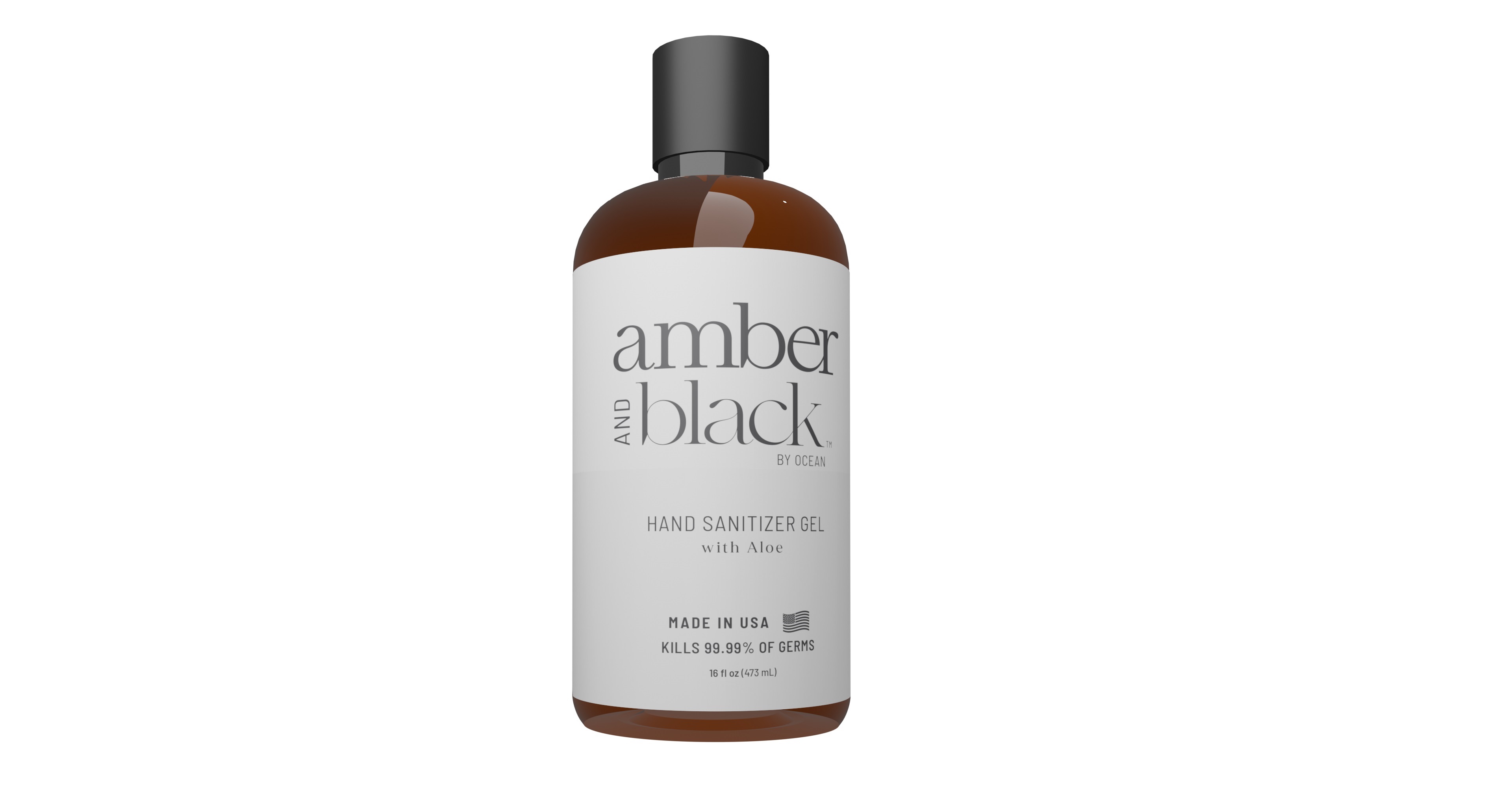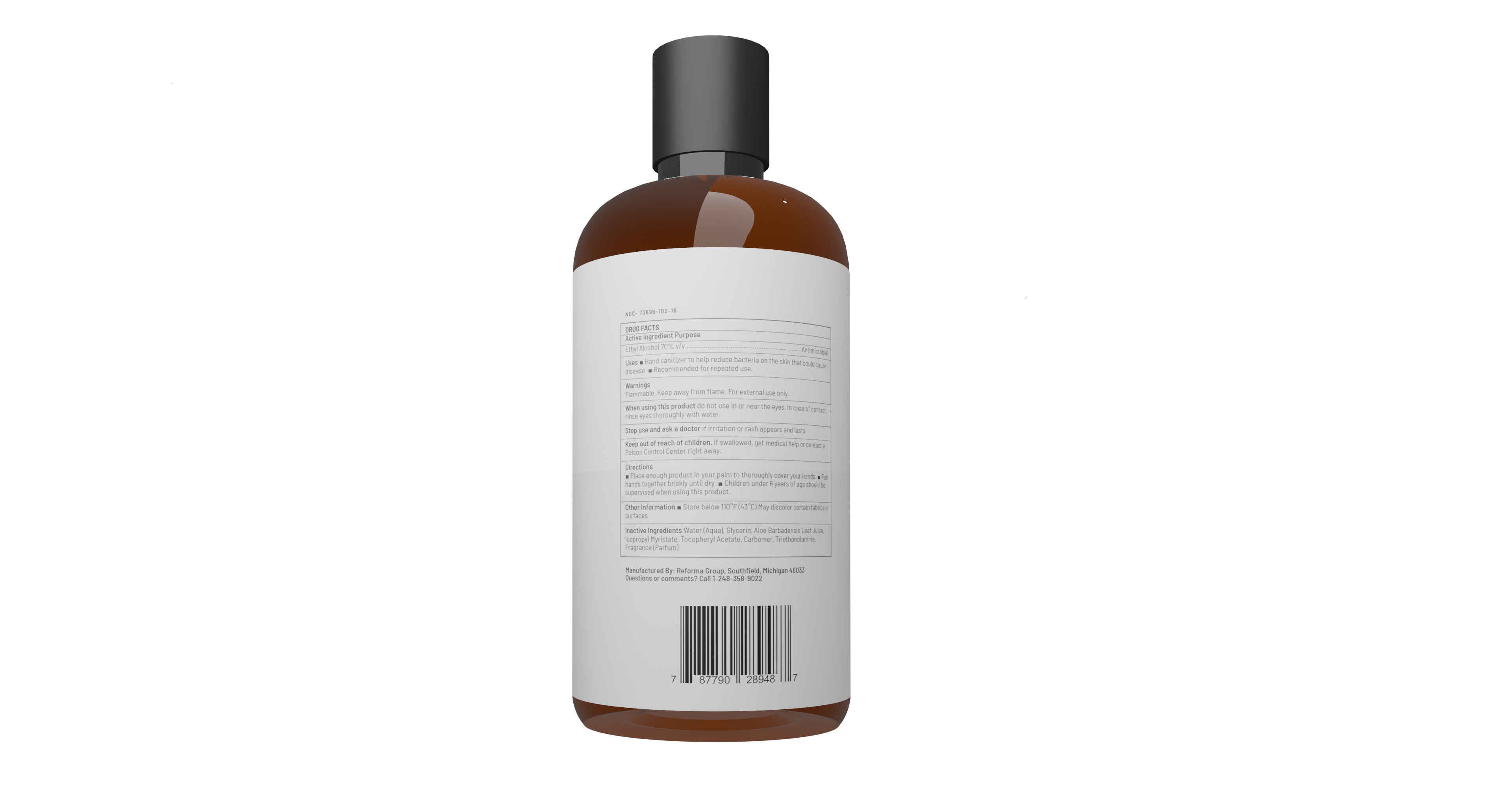 DRUG LABEL: Hand Sanitizer Gel
NDC: 73696-102 | Form: GEL
Manufacturer: NV Labs
Category: otc | Type: HUMAN OTC DRUG LABEL
Date: 20220113

ACTIVE INGREDIENTS: ALCOHOL 70 mL/100 mL
INACTIVE INGREDIENTS: WATER 29.278 mL/100 mL; .ALPHA.-TOCOPHEROL ACETATE 0.001 mL/100 mL; CARBOMER HOMOPOLYMER, UNSPECIFIED TYPE 0.35 mL/100 mL; ISOPROPYL MYRISTATE 0.25 mL/100 mL; TROLAMINE 0.12 mL/100 mL; ALOE VERA LEAF 0.001 mL/100 mL

Amber and Black HAND SANITIZER GEL (4 Fl. Oz & 16 Fl Oz.)

Active Ingredient

Active Ingredient Purpose

Ethyl Alcohol 70% v/v Antimicrobial

USES

- Hand Sanitizer to help reduce bacteria on the skin that could cause disease
- Recommended for repeated use

WARNING

Warnings

Flammable Keep away from Flame

For External Use only

When using this product do not use in or near the eyes. In case of contact, rinse eyes thoroughly with water.

Stop use and ask a doctor if irritation or rash appeara and lasts

Keep out of reach of children, If swallowed, get medical help or contact a Poison Control Center right away.

Directions

- Place enough product in your palm to thoroughly cover your hands
- Rub hands together briskly until dry
- Children under 6 years of age should be supervised when using this product

Other information

- Store below 110F (43C) May discolor certain fabrics or surfaces

In active Ingredients

Water (Aqua) , Glycerin, Aloe Barbadensis Leaf Juice, Isopropyl Myristate, Tocopheryl Acetate, Carbomer, Triethanolamine, Fragrance (Parfum)

Manufactured By: Questions or Comments

Manufactured By: Reforma Group, Southfield, Michigan 48033

Questions or comments? Call 1-248-358-9022

Keep out of Reach of Children. If swallowed , get medical help or contact a Poison Control Center right away.

Purpose

Antimicrobial

PRINCIPLE DISPLAY PANEL

Amber and Black

HAND SANITIZER GEL

MADE IN USA

NDC 73696-102-04

KILLS 99.99% of Germs

4 fl. oz (120 mL)

Amber and Black

HAND SANITIZER GEL

MADE IN USA

NDC 73696-102-16

KILLS 99.99% of Germs

16 fl.oz (473 mL)